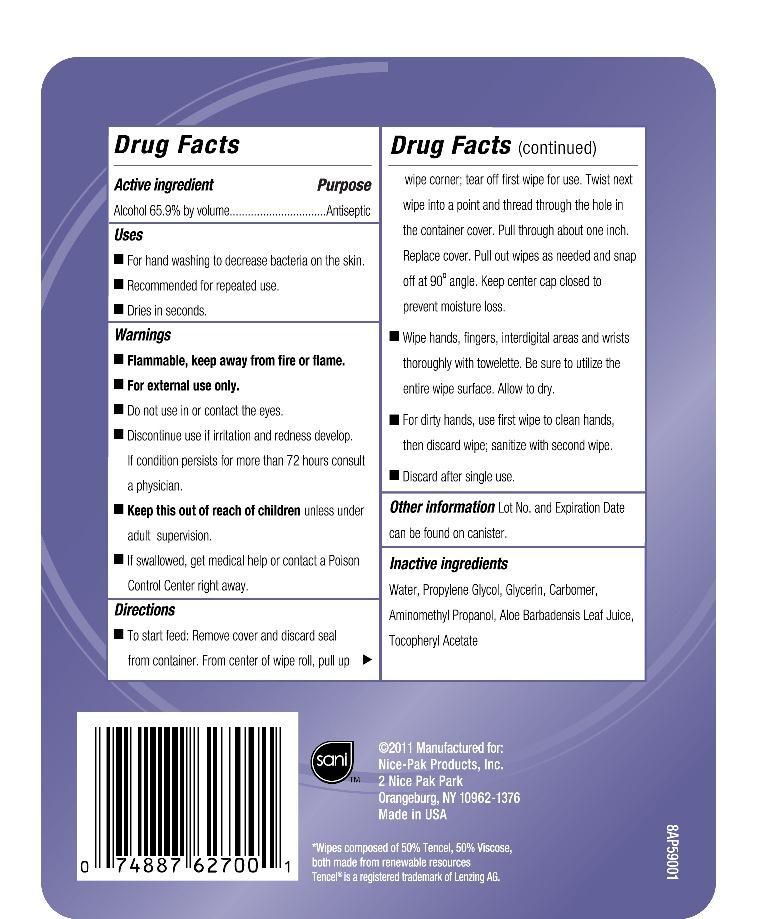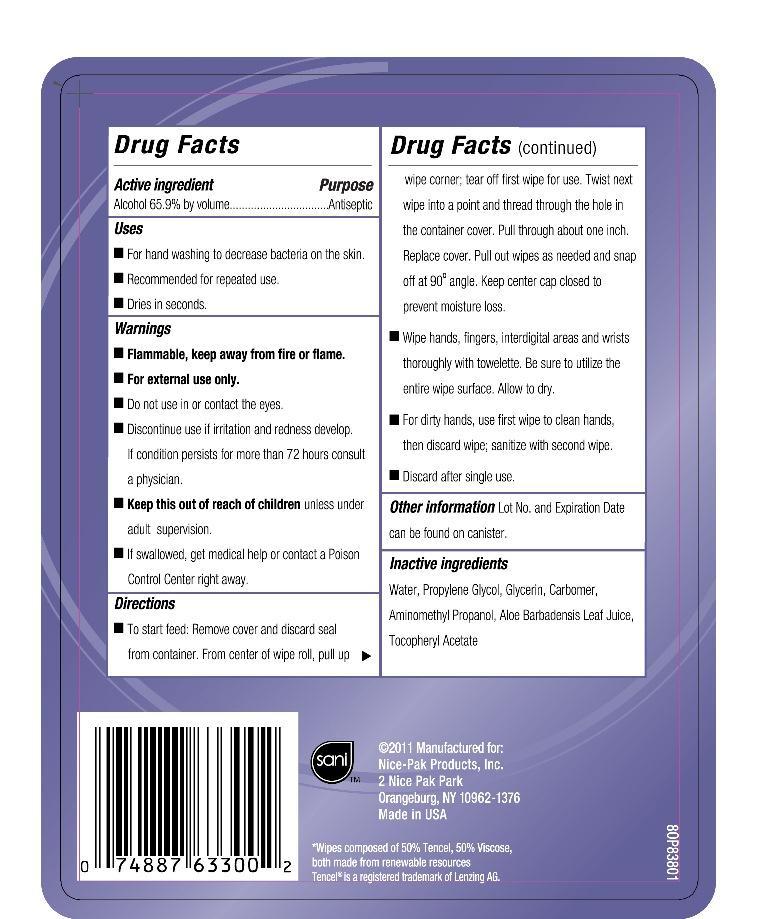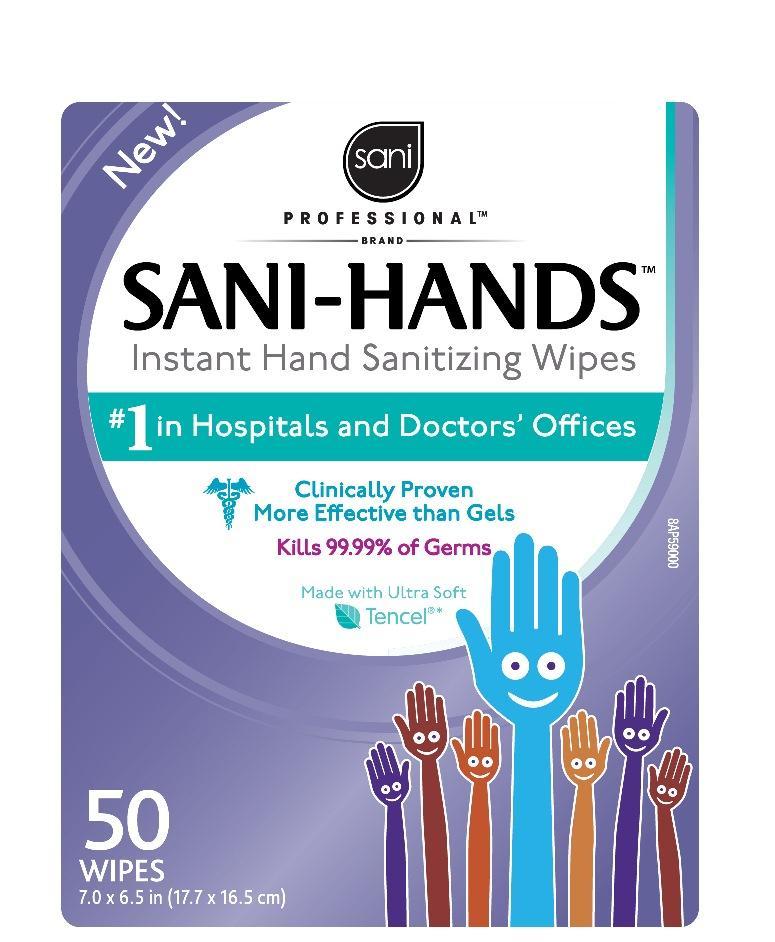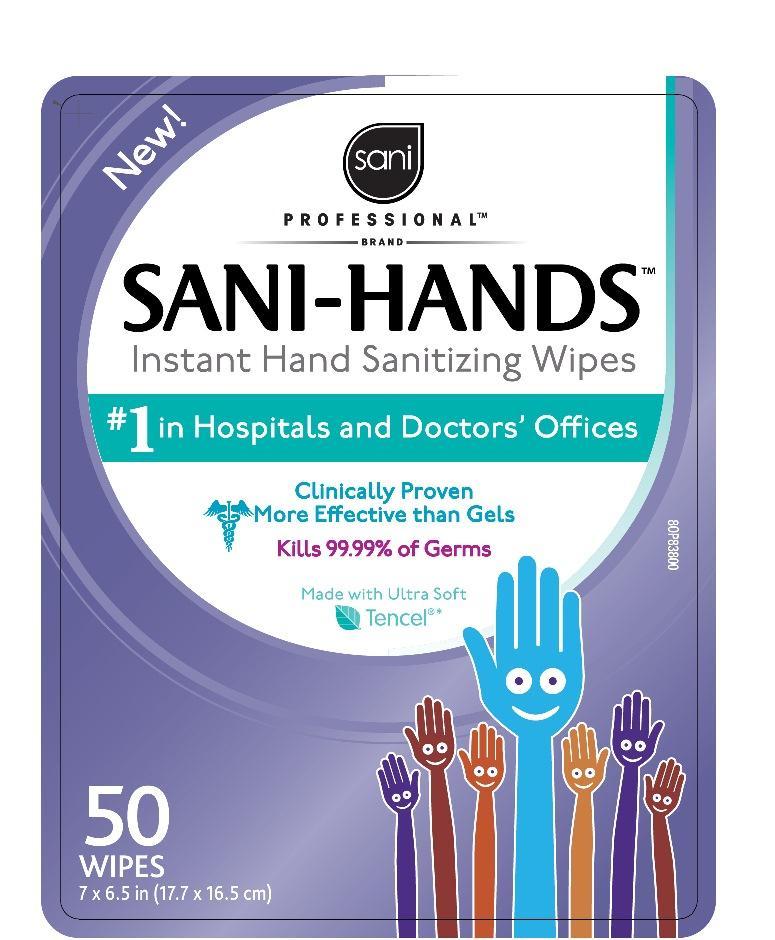 DRUG LABEL: Sani Professional Brand Sani-Hands
NDC: 10819-7005 | Form: CLOTH
Manufacturer: Profesional Disposables International, Inc.
Category: otc | Type: HUMAN OTC DRUG LABEL
Date: 20130228

ACTIVE INGREDIENTS: Alcohol 0.659 mL/1 mL
INACTIVE INGREDIENTS: WATER; PROPYLENE GLYCOL; GLYCERIN; CARBOMER HOMOPOLYMER TYPE C; AMINOMETHYL PROPANEDIOL; ALOE VERA LEAF; ALPHA-TOCOPHEROL ACETATE

SANI PROFESSIONAL BRAND SANI-HANDS INSTANT HAND SANITIZING WIPES

Uses

- For hand washing to decrease bacteria on the skin.
- Recommended for repeated use.
- Dries in seconds.

Warnings

- Flammable, keep away from fire or flame.
- For external use only.
- Do not use in or contact the eyes.
- Discontinue use if irritation and redness develop. If condition persist for more than 72 hours consult a physician.
- If swallowed, get medical help or contact a Poison Control Center right away.

KEEP OUT OF REACH OF CHILDREN

- Keep this out of reach of children unless under adult supervision.

Directions

- To start feed: Remove cover and discard seal from container. From center of wipe roll, pull up wipe corner; tear off first wipe for use. Twist next wipe into a point and thread through the hole in the container cover. Pull through about one inch. Replace cover. Pull out wipes as needed and snap off at 90o angle. Keep center cap closed to prevent moisture loss.
- Wipe hands, fingers, interdigital areas and wrists thoroughly with towelette. Be sure to utilize the entire wipe surface. Allow to dry.
- For dirty hands, use first wipe to clean hands, then discard wipe; sanitize with second wipe.
- Discard after single use.

Other information

Lot No. and Expiration Date can be found on canister

Dosage

For dirty hands, use first wipe to clean hands, then discard wipe; sanitize with second wipe. Discard after single use.

Inactive ingredients

Water, Propylene Glycol, Glycerin, Carbomer, Aminometyl Propanol, Aloe Barbadensis Leaf Juice, Tocopheryl Acetate

Manufactured for:
Nice-Pak Products, Inc.
2 Nice-Pak Park
Orangeburg, NY 10962-1376 - Made in USA - 1-800-999-6423

*Wipes composed of 50% Tencel, 50% Viscose, both made from renewable resources

Tencel is a registered trademark of Lenzing AG.

Principal Display Panel - 300 Count Canister

Sani

Professional Brand

SANI-HANDS(R) for Kids

- Instant Hands Sanitizing Wipes
- Clinically Proven More Effective than Gels
- Kills 99.99% of Germs
- Made with Ultra Soft Tencel(R)*

50 WIPES
7.0 x 6.5 in (17.7 x 16.5 cm)
Front Canister1 Label
Back Canister1 Label
Front Canister2 Label
Back Canister2 Label

Active ingredient

Alcohol 65.9% by volume

Purpose

Antiseptic